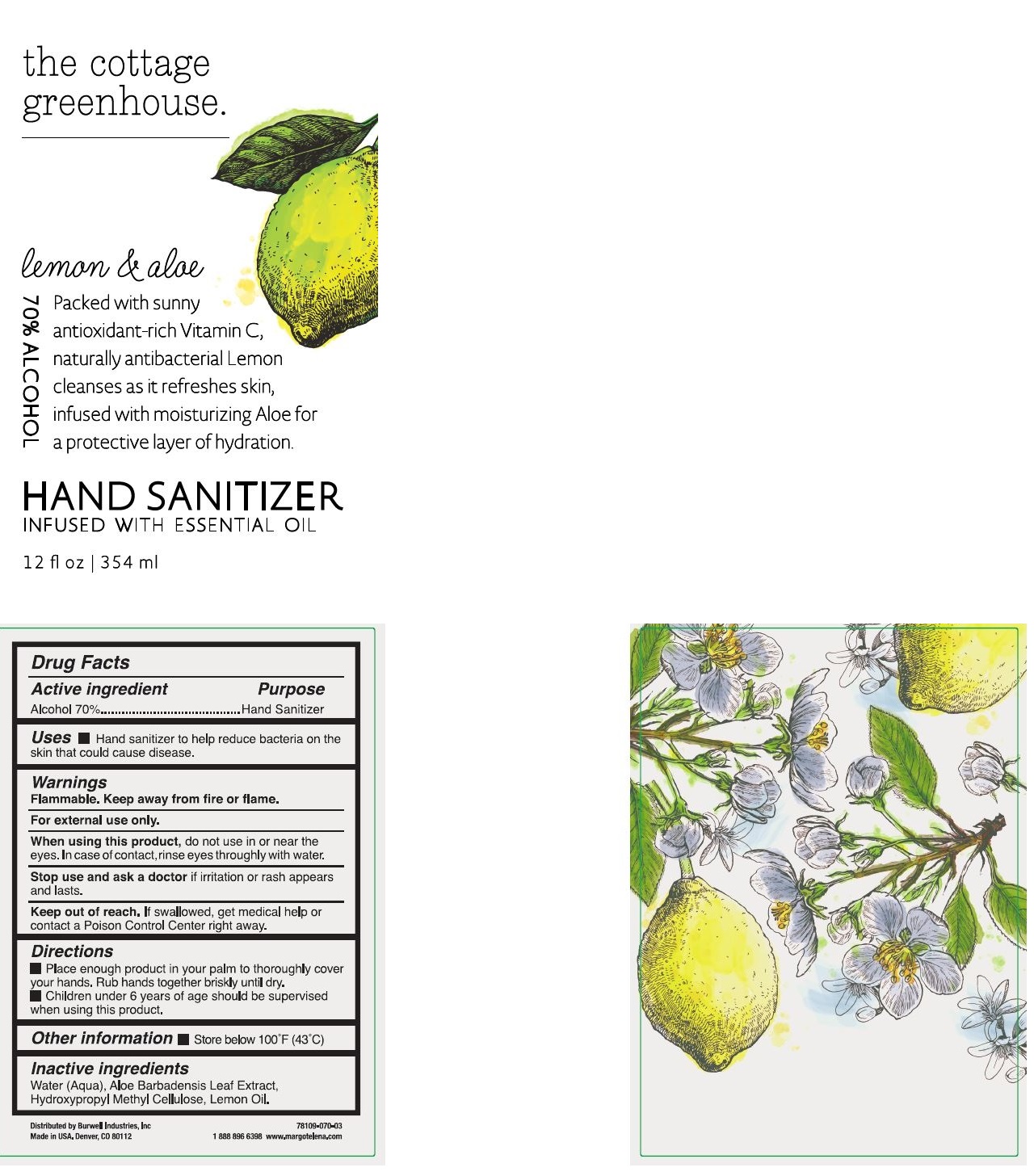 DRUG LABEL: Hand Sanitizer-Citrus Garden
NDC: 78109-070 | Form: GEL
Manufacturer: Burwell Industries, Inc.
Category: otc | Type: HUMAN OTC DRUG LABEL
Date: 20200817

ACTIVE INGREDIENTS: ALCOHOL 70 mL/100 mL
INACTIVE INGREDIENTS: HYPROMELLOSES 0.75 mL/100 mL; WATER 28.85 mL/100 mL; ALOE VERA LEAF POLYSACCHARIDES 0.1 mL/100 mL; LEMON OIL 0.3 mL/100 mL

Hand Sanitizer - Antibacterial Hand Sanitizer

Active ingredient

Alcohol 70%

Purpose

Hand Sanitizer

Use

Hand Sanitizer to help reduce bacteria on the skin that could cause disease.

Warnings

Flammable, Keep away from fire or flame.

For External Use only.

When Using this product.

do not use in or near the eyes, in case of contact, rinse throughly with water.

Stop Using this product.

if irritation or rash appears and lasts.

Keep out of Reach of Children

if Swallowed, get medical help or contact a Poison Control Center right away.

Directions

- Place enough product in your palm to throoughly cover your hands. Rub hands together briskly until dry.
- Children under 6 years of age should be supervised when using this product.

Other information

- Store below 110°F (43°C)

Ingredients

Alcohol, Water, Acrylates(C-10/30 Alkyl Acylate) Crosspolymer, Aloe Vera, Triethanolamine.

Package Label - Principal Disaplay Label

354 mL NDC: 78109-070-03